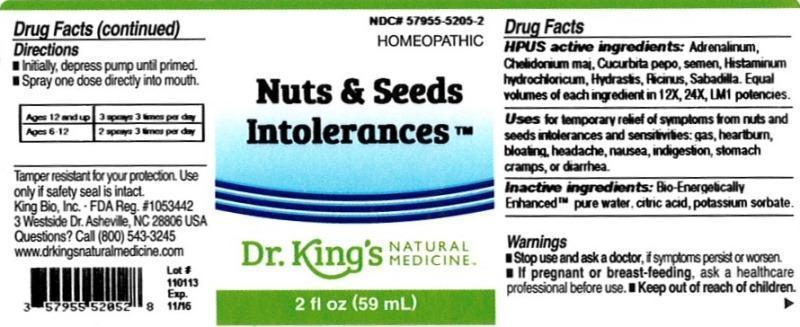 DRUG LABEL: Nuts and Seeds Intolerances
NDC: 57955-5205 | Form: LIQUID
Manufacturer: King Bio Inc.
Category: homeopathic | Type: HUMAN OTC DRUG LABEL
Date: 20131125

ACTIVE INGREDIENTS: EPINEPHRINE 12 [hp_X]/59 mL; CHELIDONIUM MAJUS 12 [hp_X]/59 mL; PUMPKIN SEED 12 [hp_X]/59 mL; HISTAMINE DIHYDROCHLORIDE 12 [hp_X]/59 mL; GOLDENSEAL 12 [hp_X]/59 mL; RICINUS COMMUNIS SEED 12 [hp_X]/59 mL; SCHOENOCAULON OFFICINALE SEED 12 [hp_X]/59 mL
INACTIVE INGREDIENTS: WATER; CITRIC ACID MONOHYDRATE; POTASSIUM SORBATE

Nut and Seeds Intolerances™

ACTIVE INGREDIENT

Drug Facts__________________________________________________________________________________________________________

HPUS active ingredients: Adrenalinum, Chelidonium majus, Cucurbita pepo, semen, Histaminum hydrochloricum, Hydrastis canadensis, Ricinus communis, Sabadilla. Equal volumes of each ingredient in 12X, 24X, LM1 potencies.

INDICATIONS AND USAGE

Uses for temporary relief of symptoms from nuts and seeds intolerances and sensitivities: gas, heartburn, bloating, headache, nausea, indigestion, stomach cramps, or diarrhea.

Inactive Ingredients:

Bio-Energetically Enhanced™ pure water, citric acid and potassium sorbate.

Warnings

- Stop use and ask your doctor if symptoms persist or worsen.

- If pregnant or breast-feeding, ask a healthcare professional before use.

- Keep out of reach of children

Directions

- Initially, depress pump until primed.
- Spray one dose directly into mouth.
- Ages 12 and up- 3 sprays 3 times per day.
- Ages 6-12- 2 sprays 3 times per day.

OTHER SAFETY INFORMATION

Tamper resistant for your protection. Use only if safety seal is intact.

PURPOSE

Uses for temporary relief of symptoms from nuts and seeds intolerances and sensitivities:

- gas
- heartburn
- bloating
- headache
- nausea
- indigestion
- stomach cramps
- diarrhea